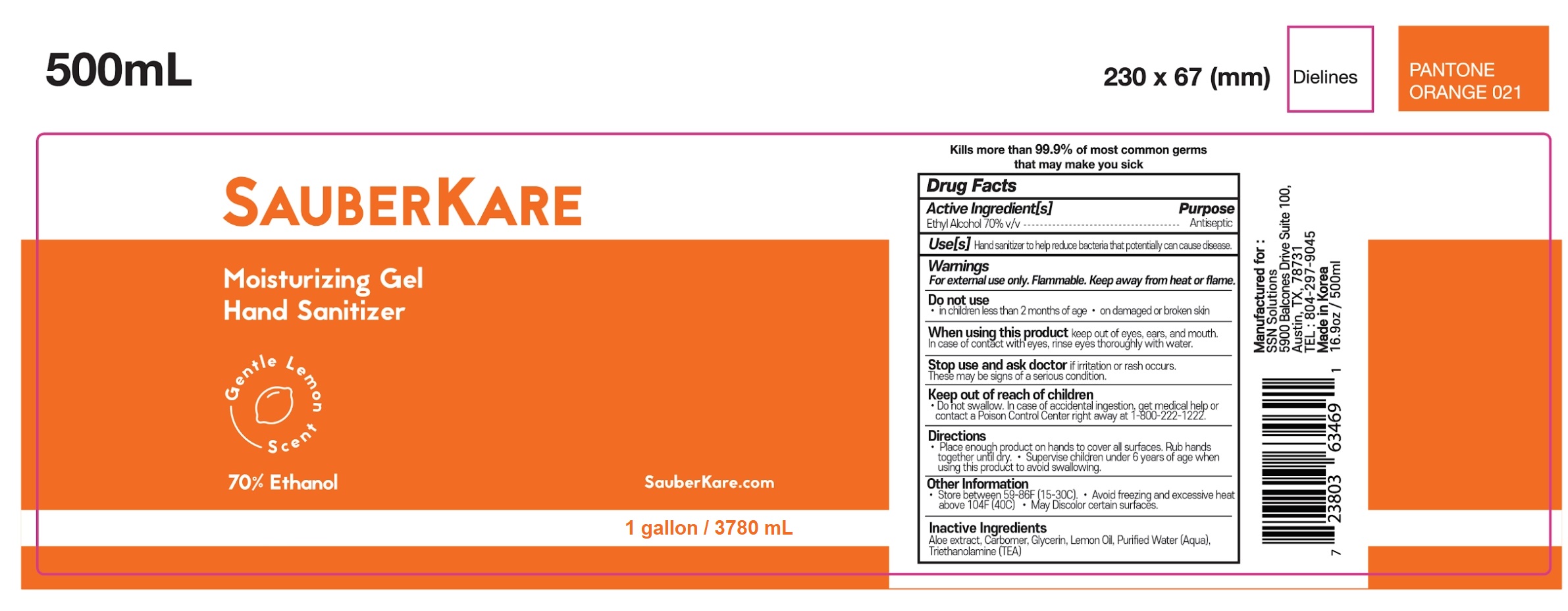 DRUG LABEL: SAUBER KARE 1 gallon
NDC: 80704-101 | Form: GEL
Manufacturer: SSN Solutions LLC
Category: otc | Type: HUMAN OTC DRUG LABEL
Date: 20220106

ACTIVE INGREDIENTS: ALCOHOL 70 mL/100 mL
INACTIVE INGREDIENTS: CARBOMER 934; GLYCERIN; WATER; TROLAMINE; ALOE; LEMON OIL

SAUBER KARE 1 gallon

Active ingredient

Ethanol 70%

Uses

Hand sanitizer to help reduce bacteria that potentially can cause disease. For use when soap and water are not available.

Purpose

Antibacterial

Warnings

For external use only. Flammable. Keep away from heat or flame.

Do not use

- in children less than 2 months of age
- on open skin wounds

When using this product

avoid contact with eyes, ears and mouth. In case of contact with eyes, rinse eyes thoroughly with water.

Stop use and ask a doctor if

irritation or rash occurs. These may be signs of a serious condition.

Keep out of reach of children. If swallowed, get medical help or contact a Poison Control Center (1-800-222-1222) right away.

Directions

- Place enough product on hands to cover all surfaces. Rub hands together until dry.
- Supervise Children under 6 years of age when using this product to avoid swallowing.

Inactive ingredients

Glycerin, Carbomer, Triethanol Amine, Aloe extract, Lemon oil, Purified water.

Keep out of reach of children. If swallowed, get medical help or contact a Poison Control Center (1-800-222-1222) right away.